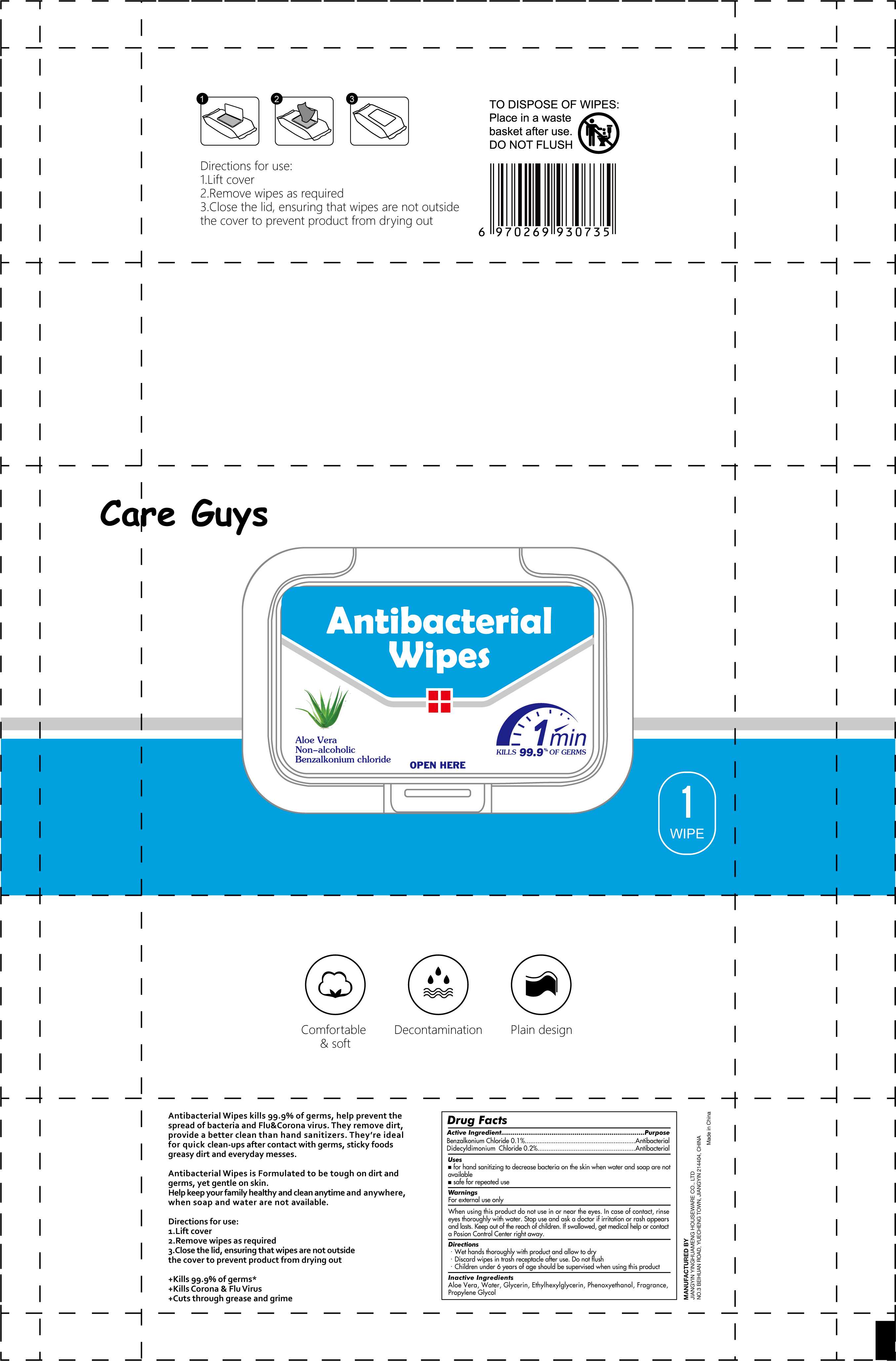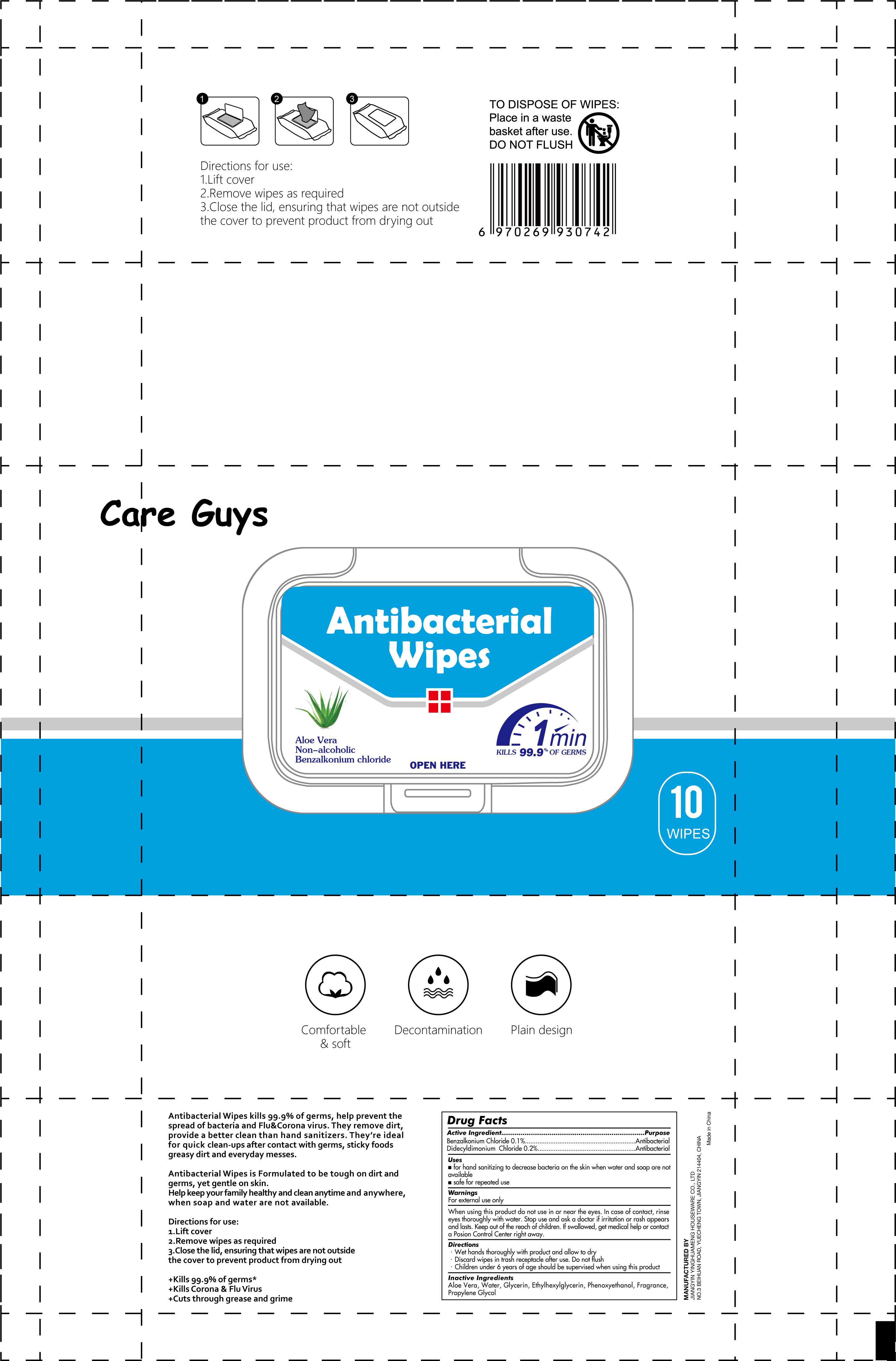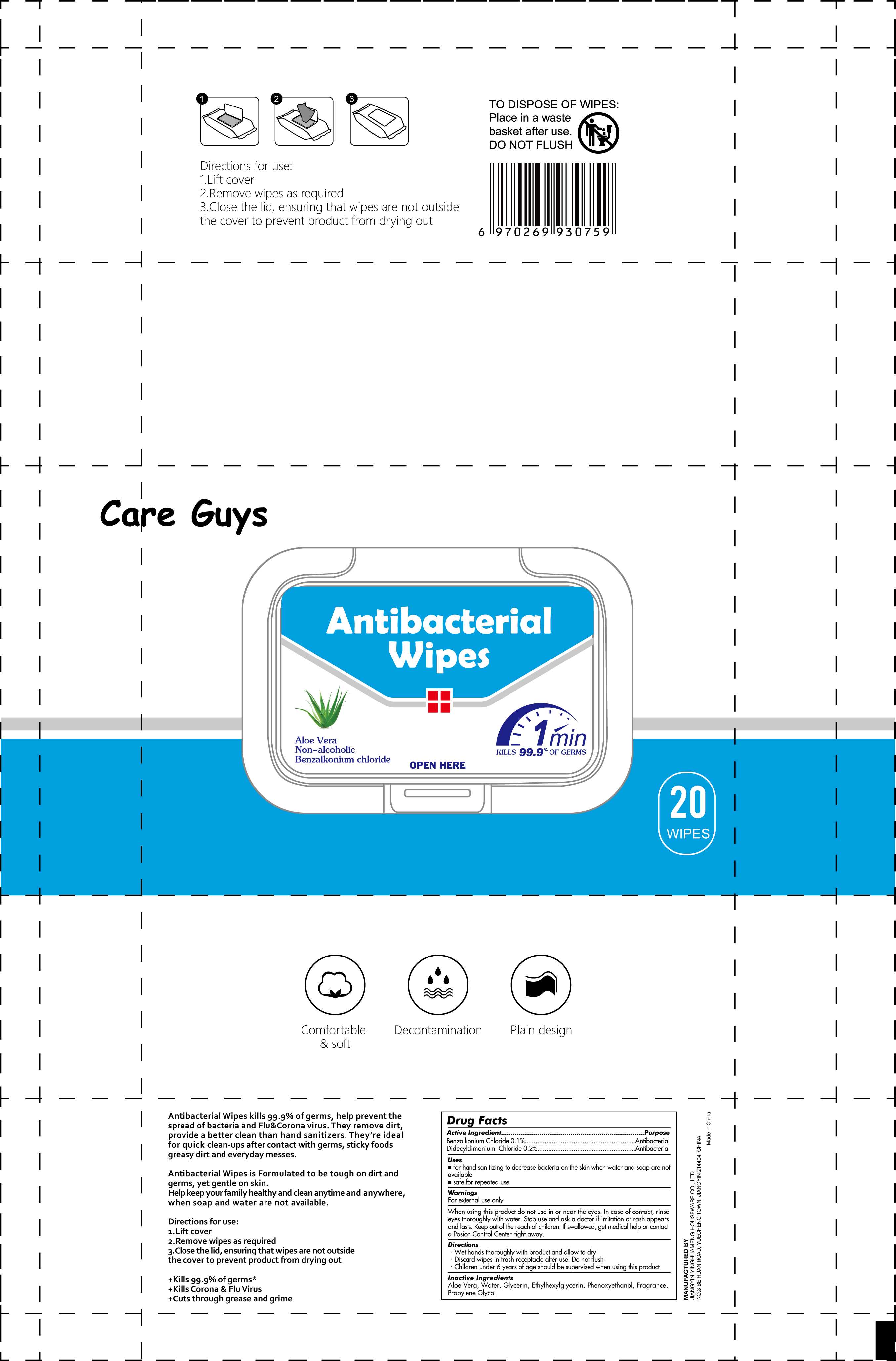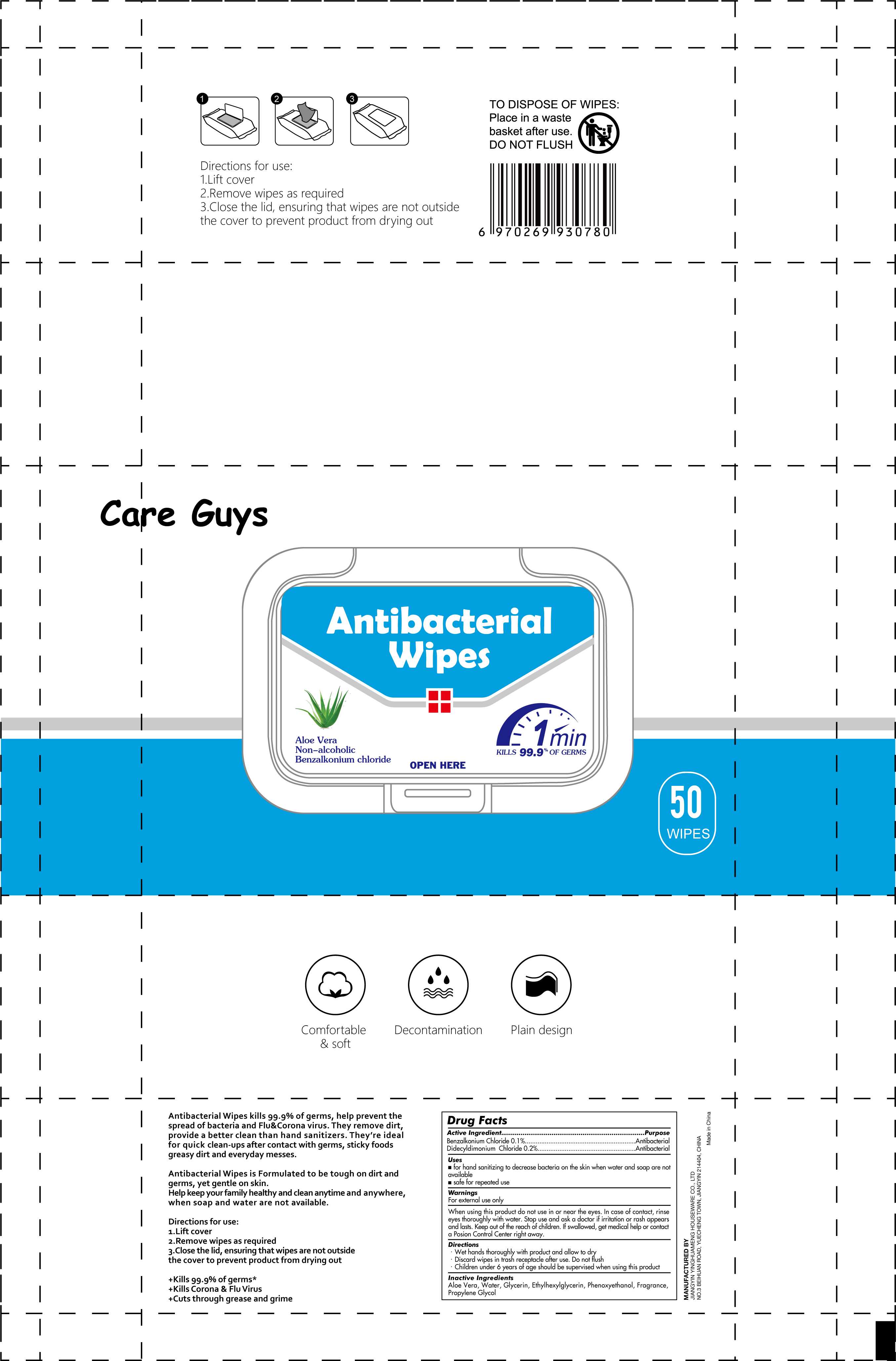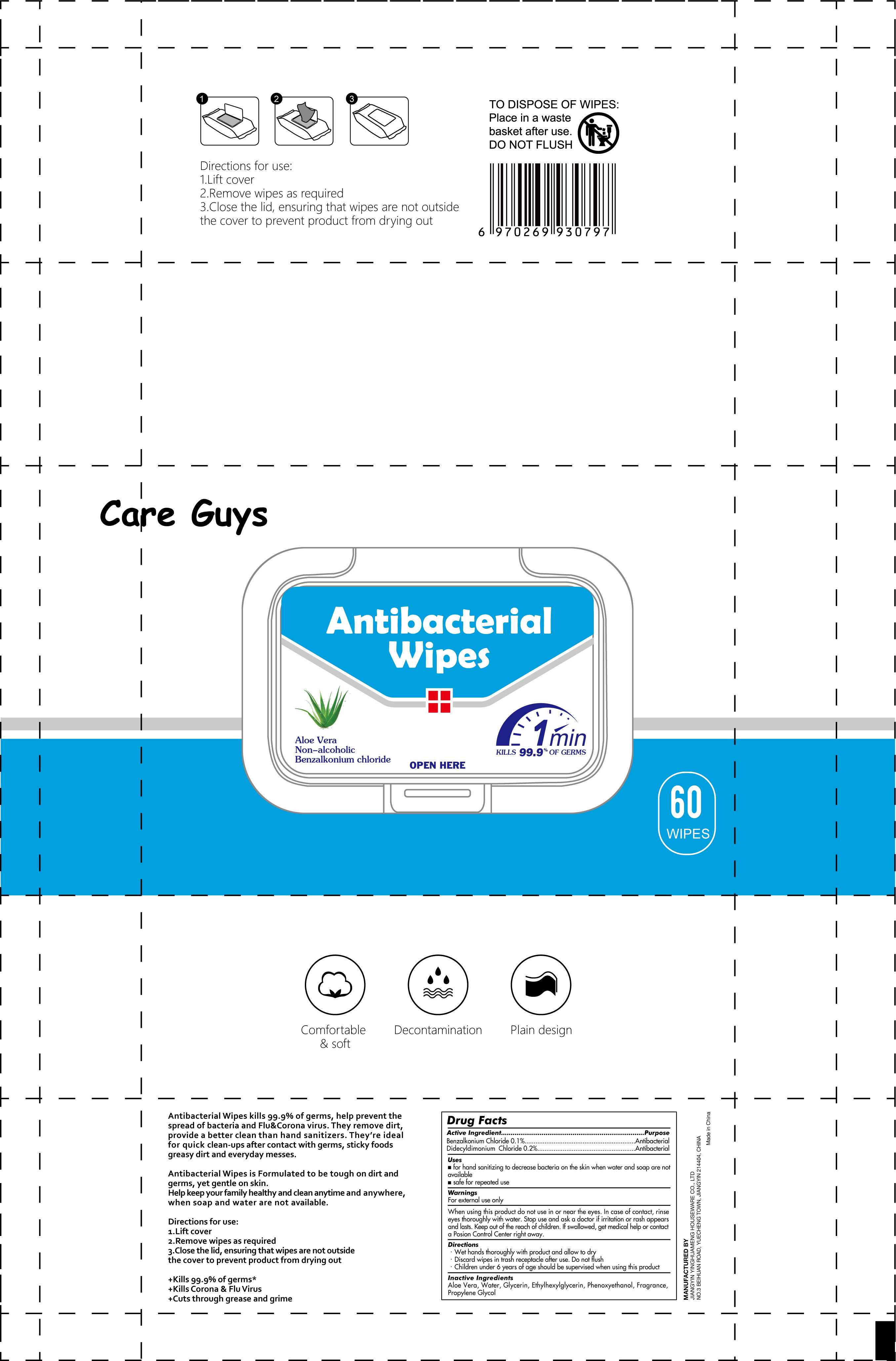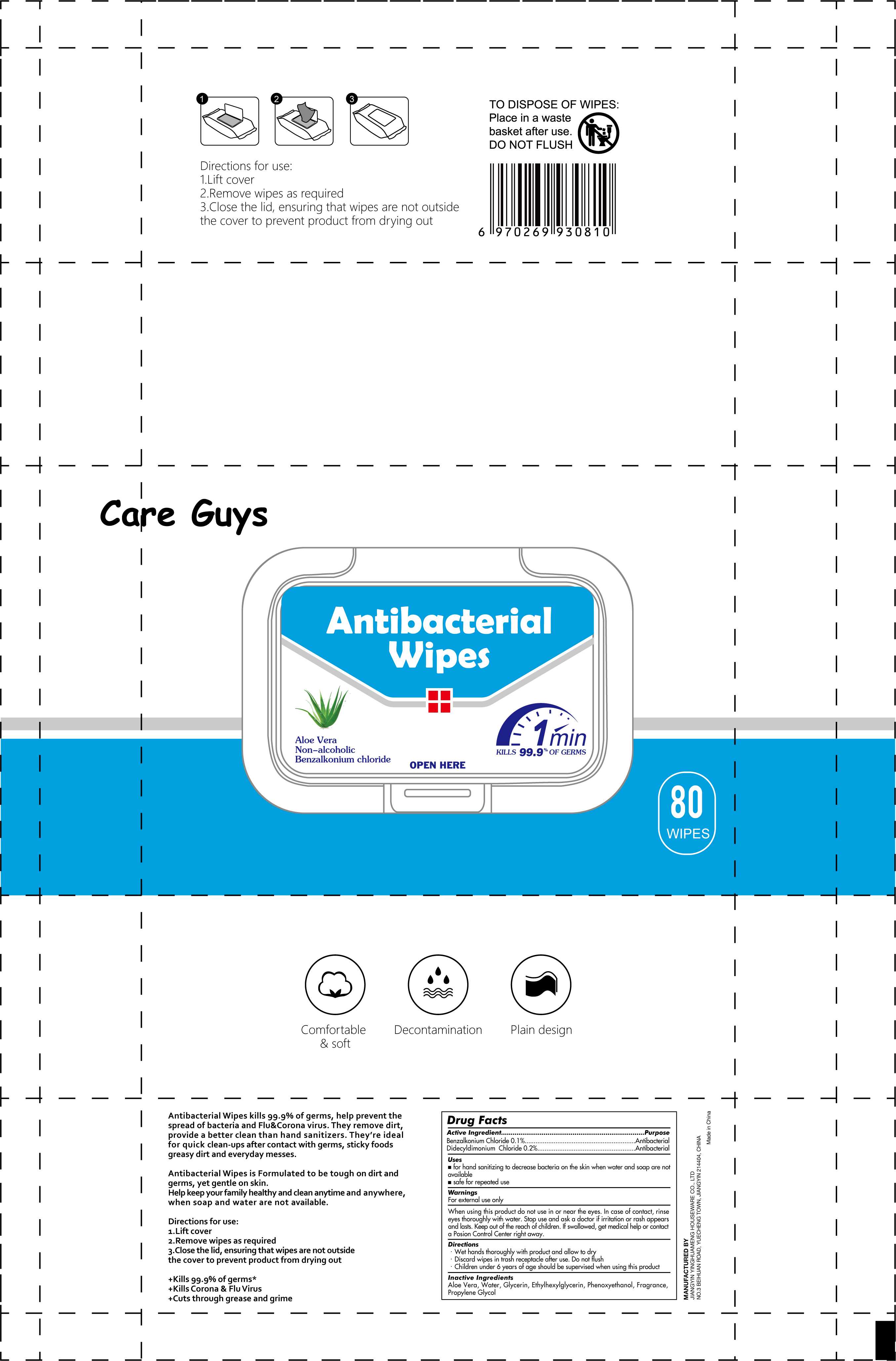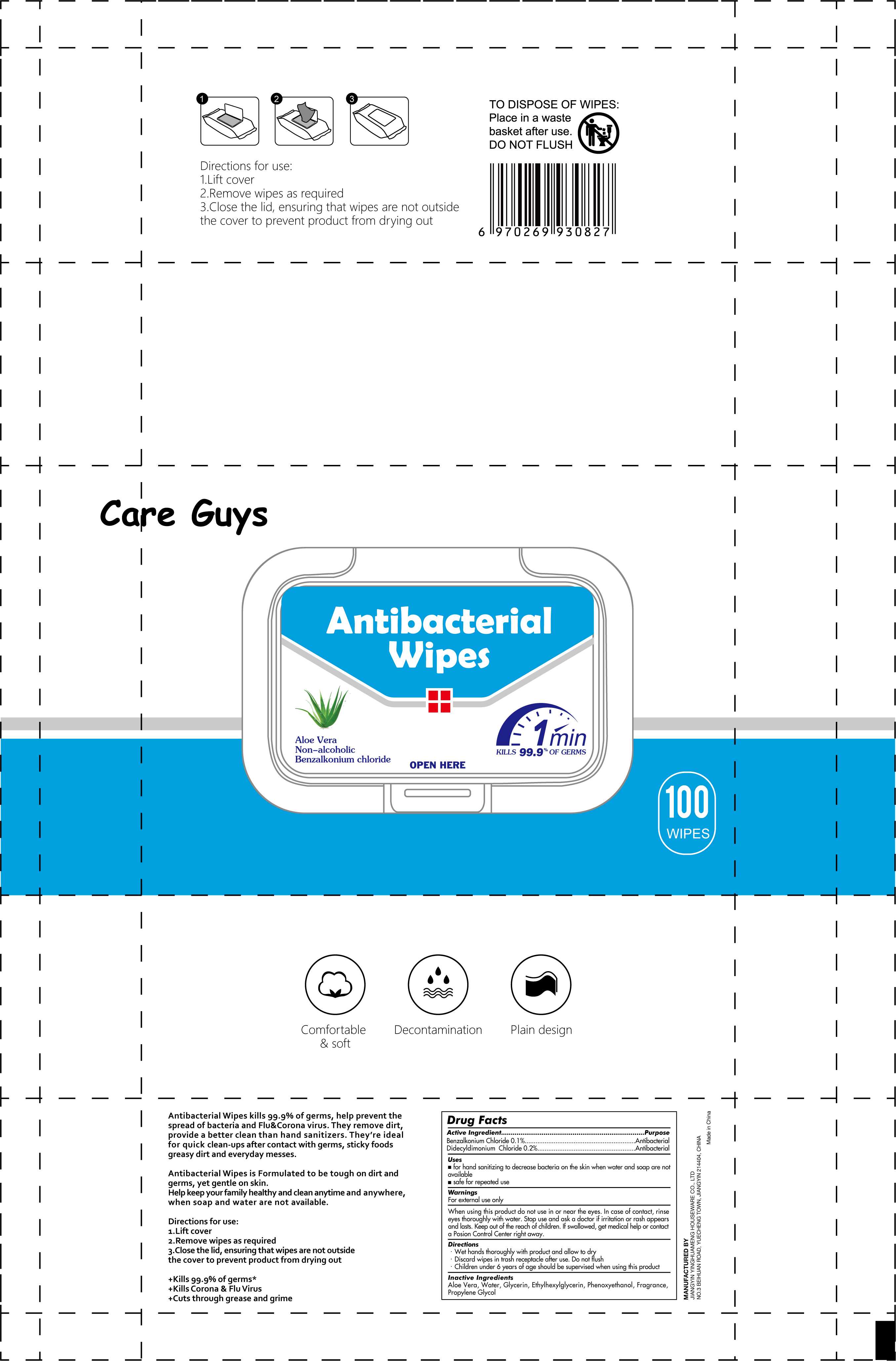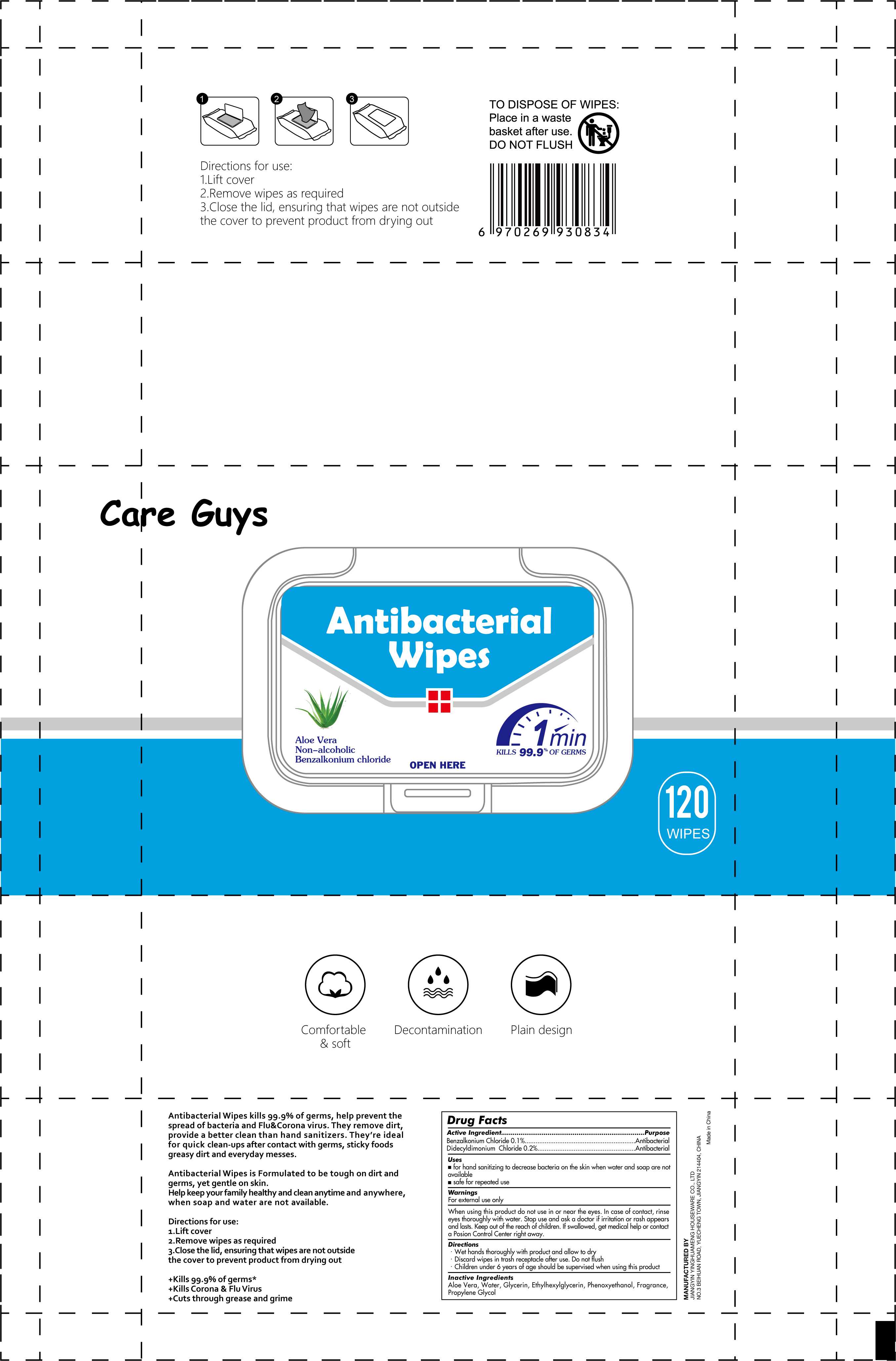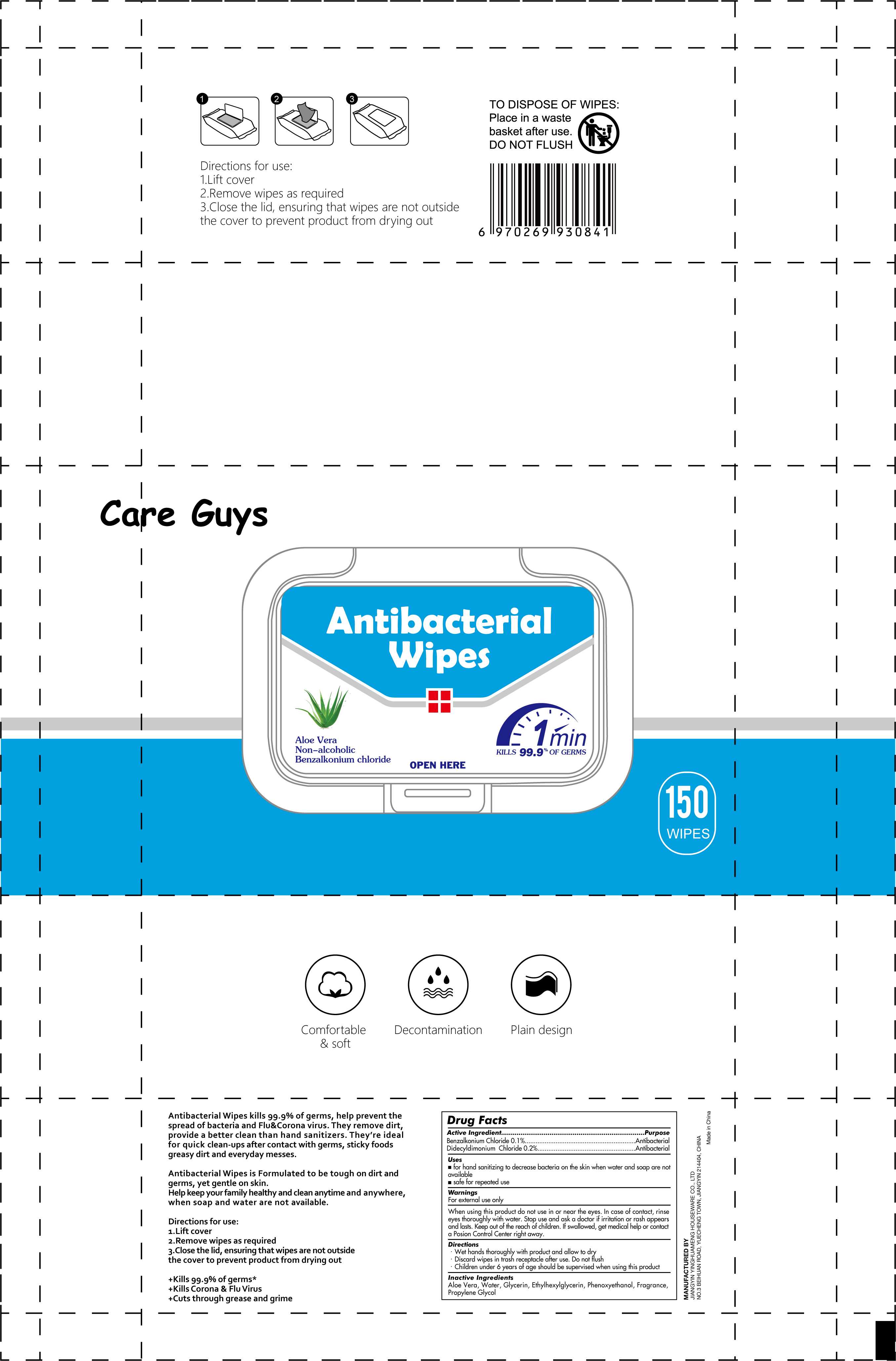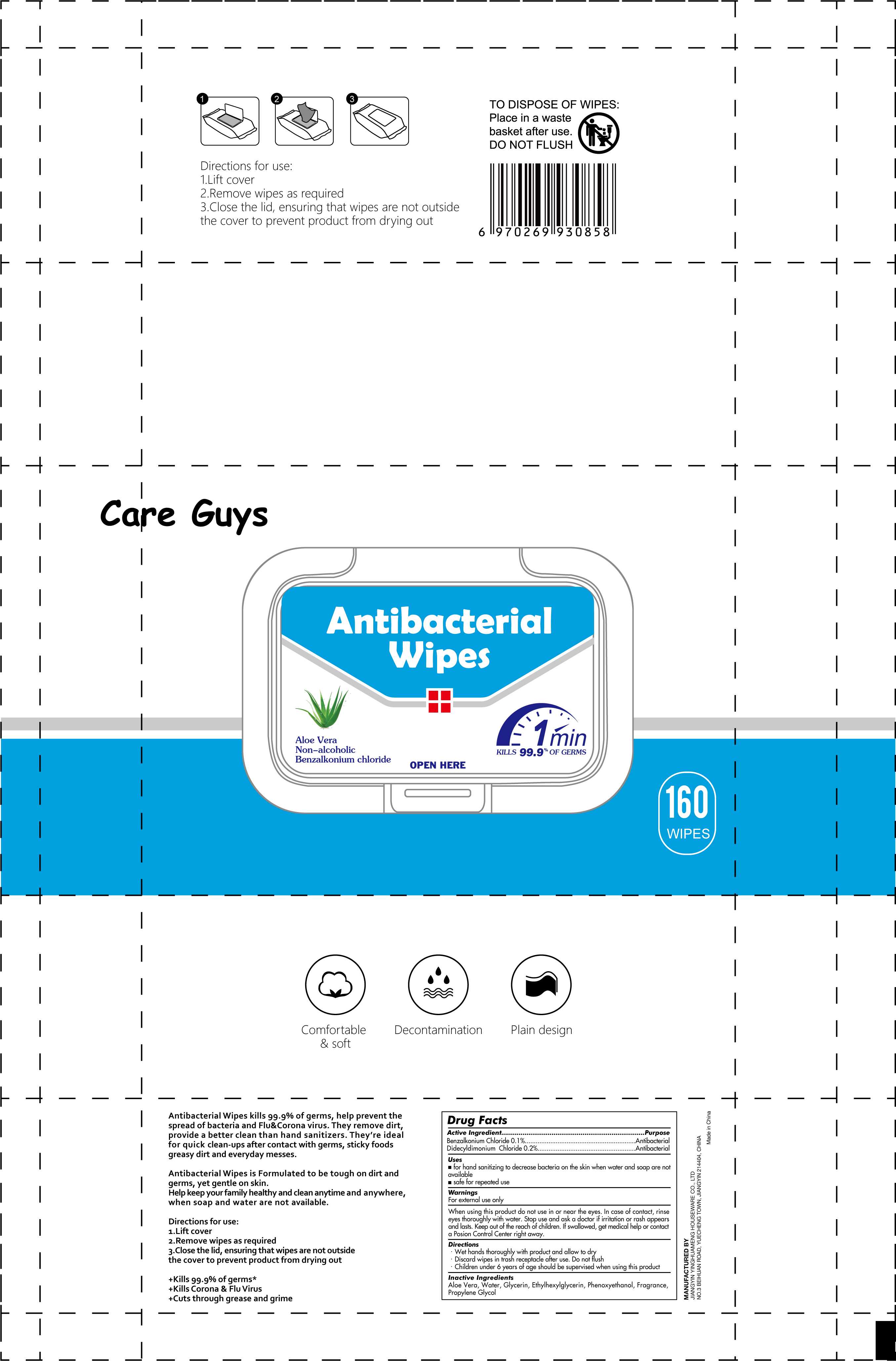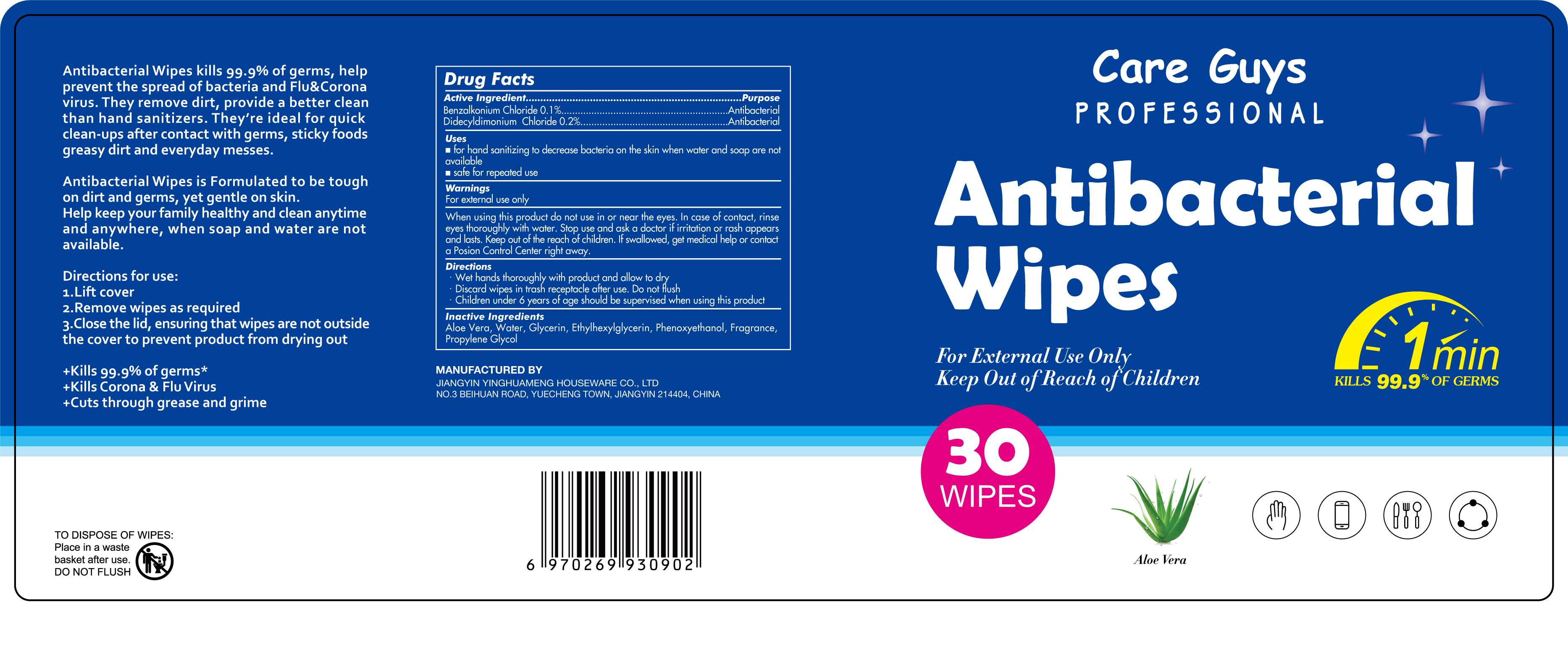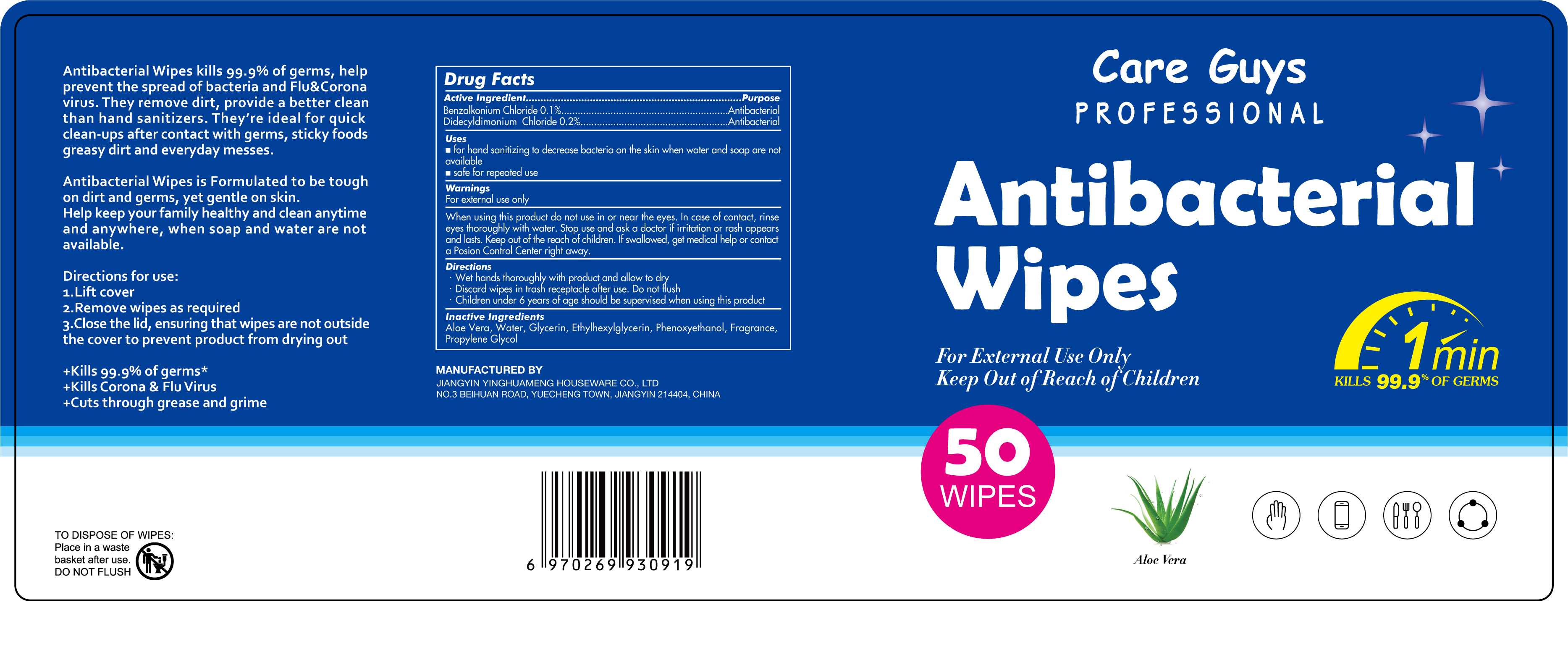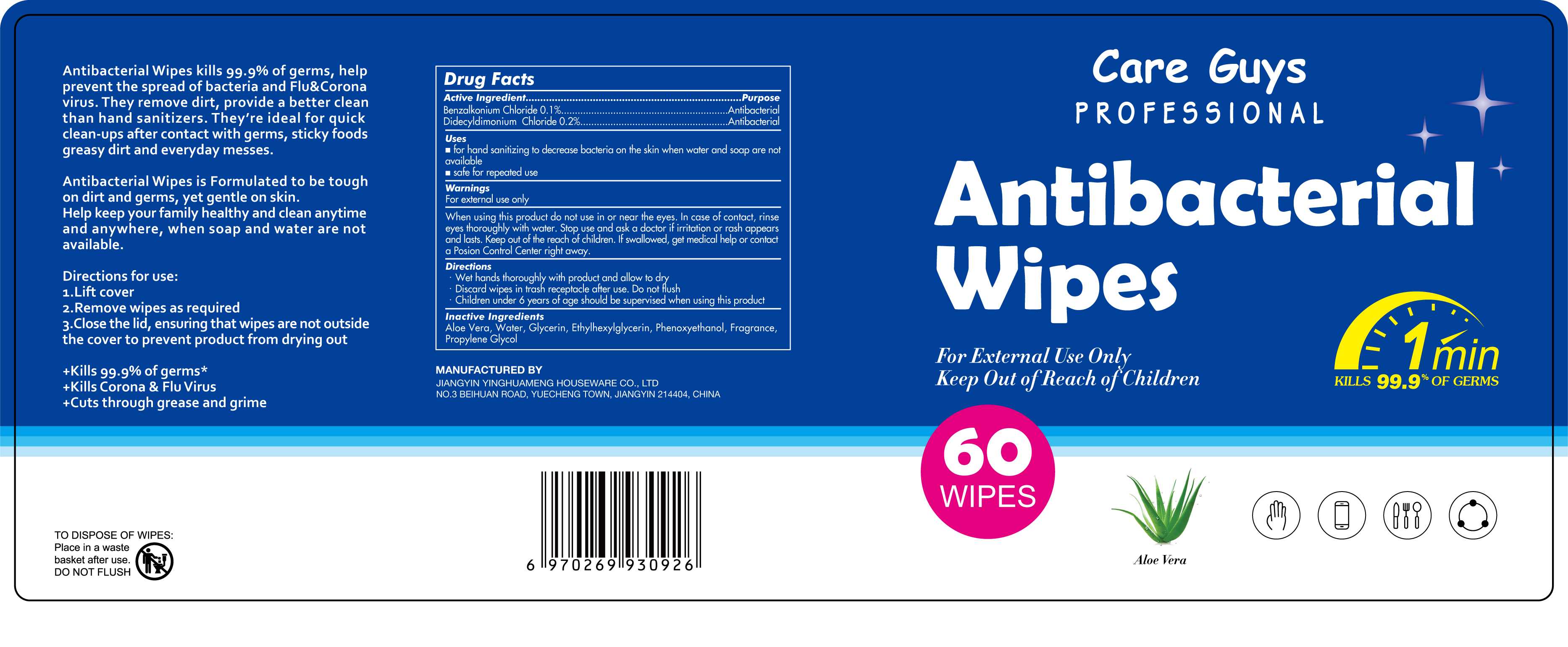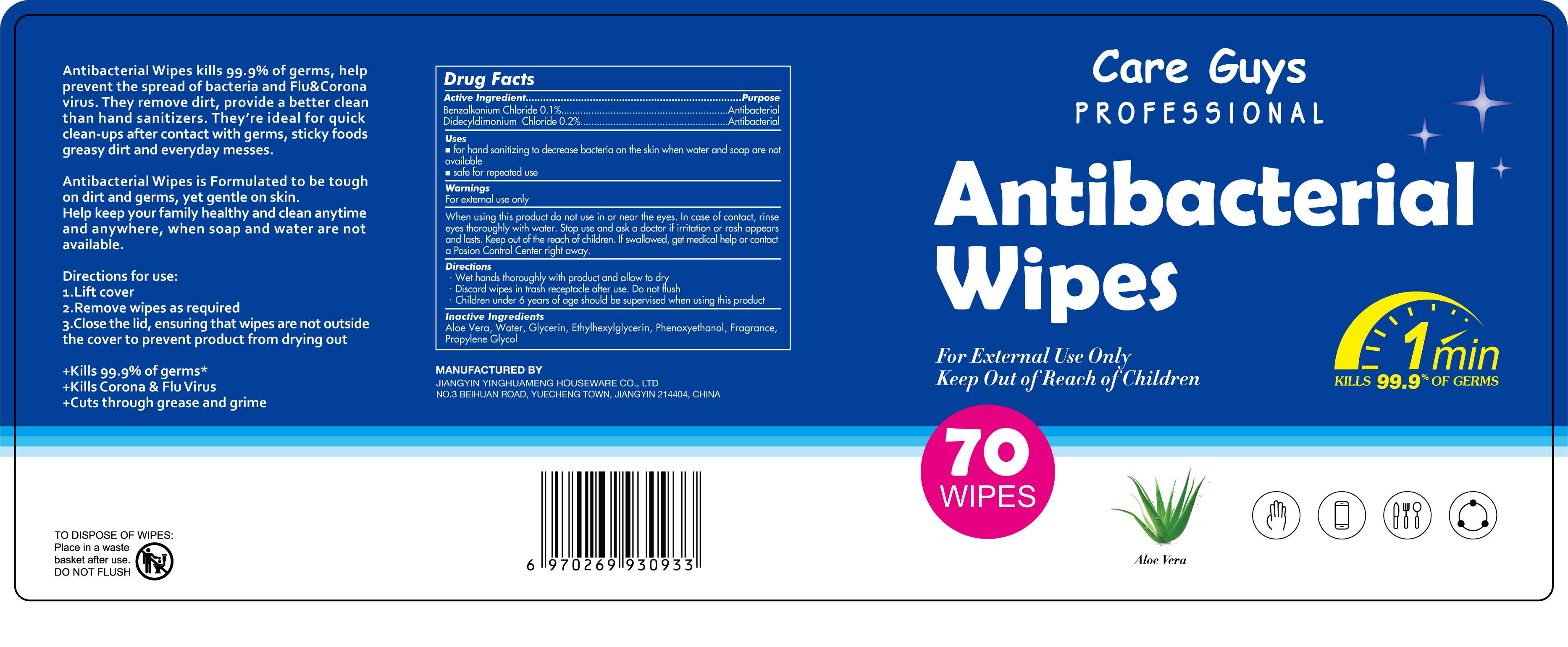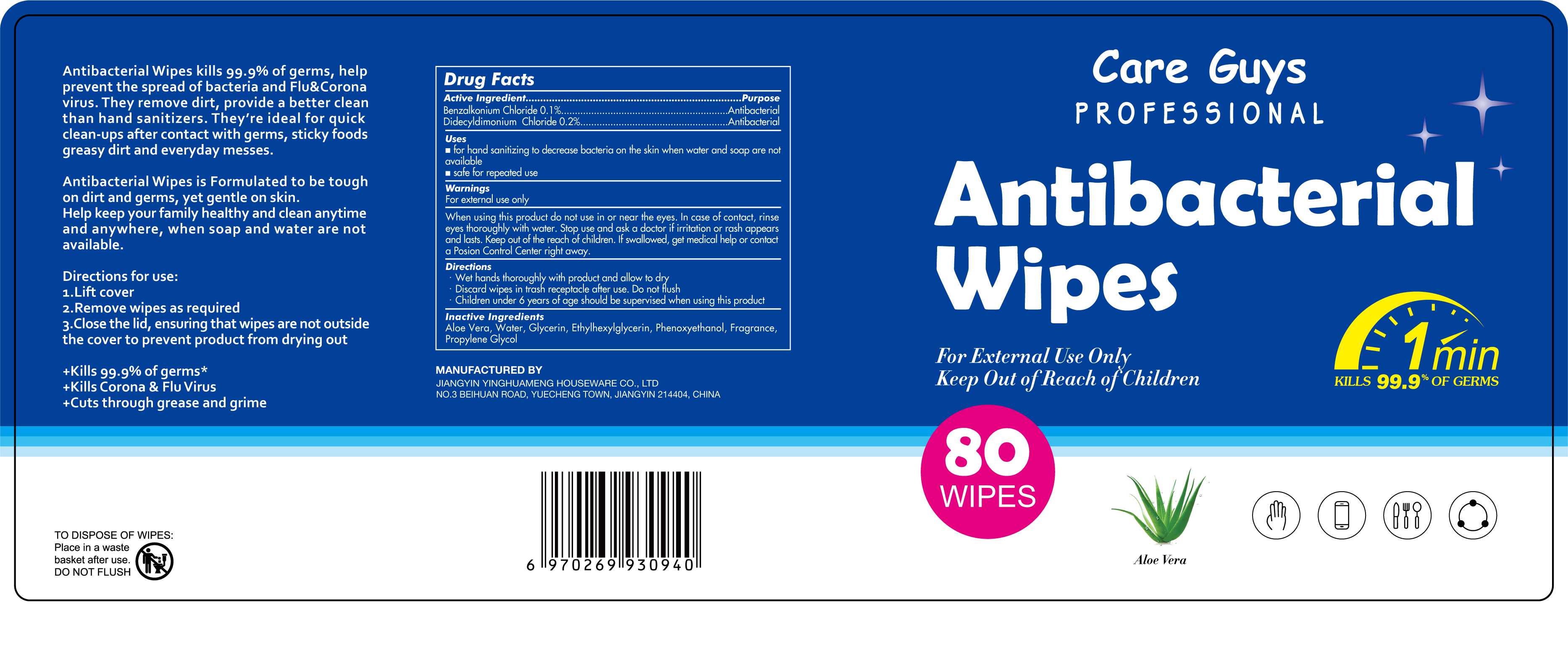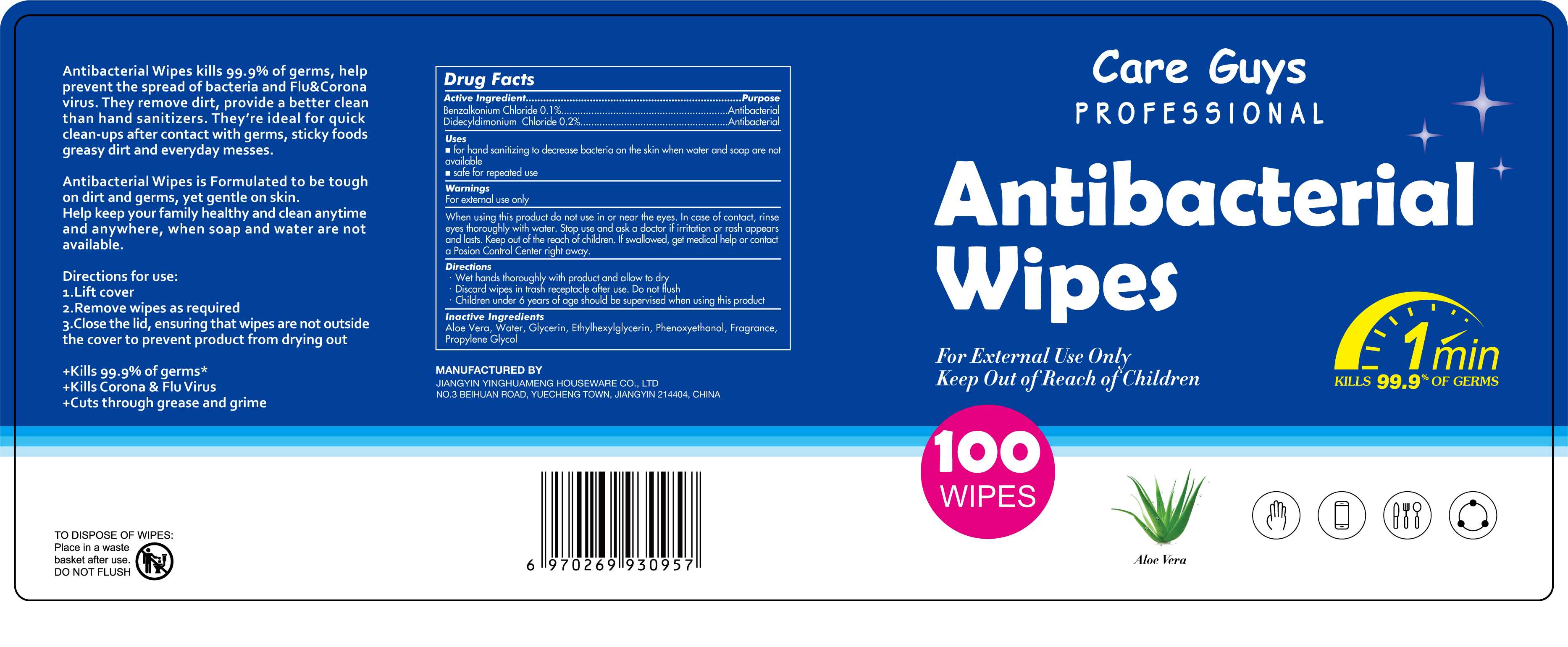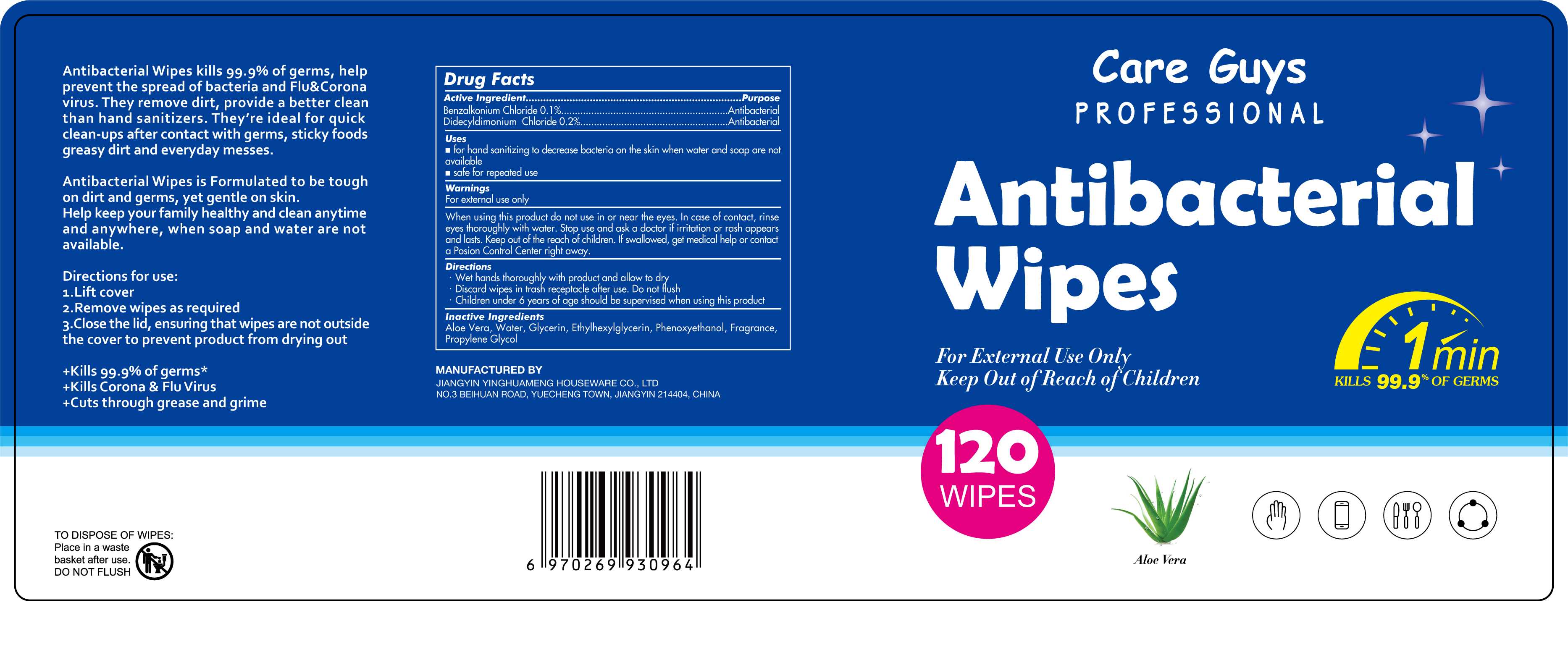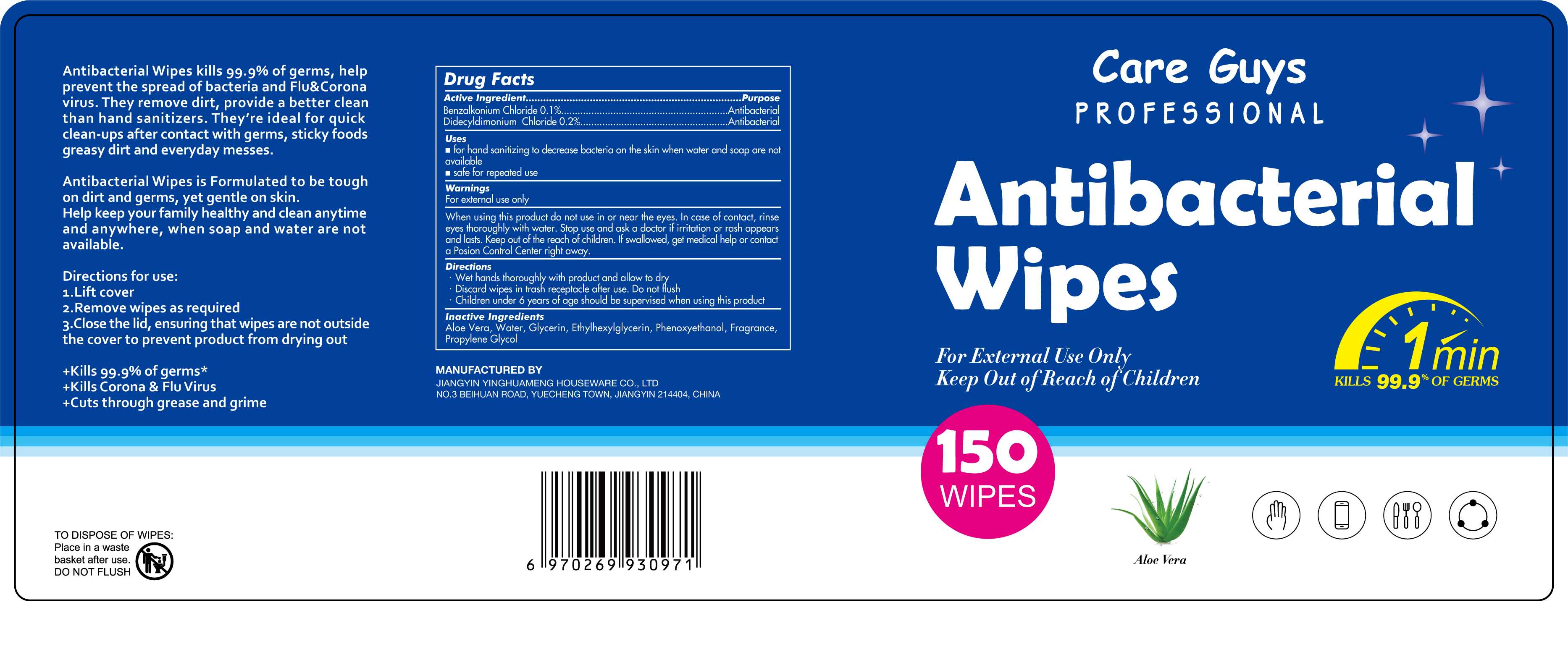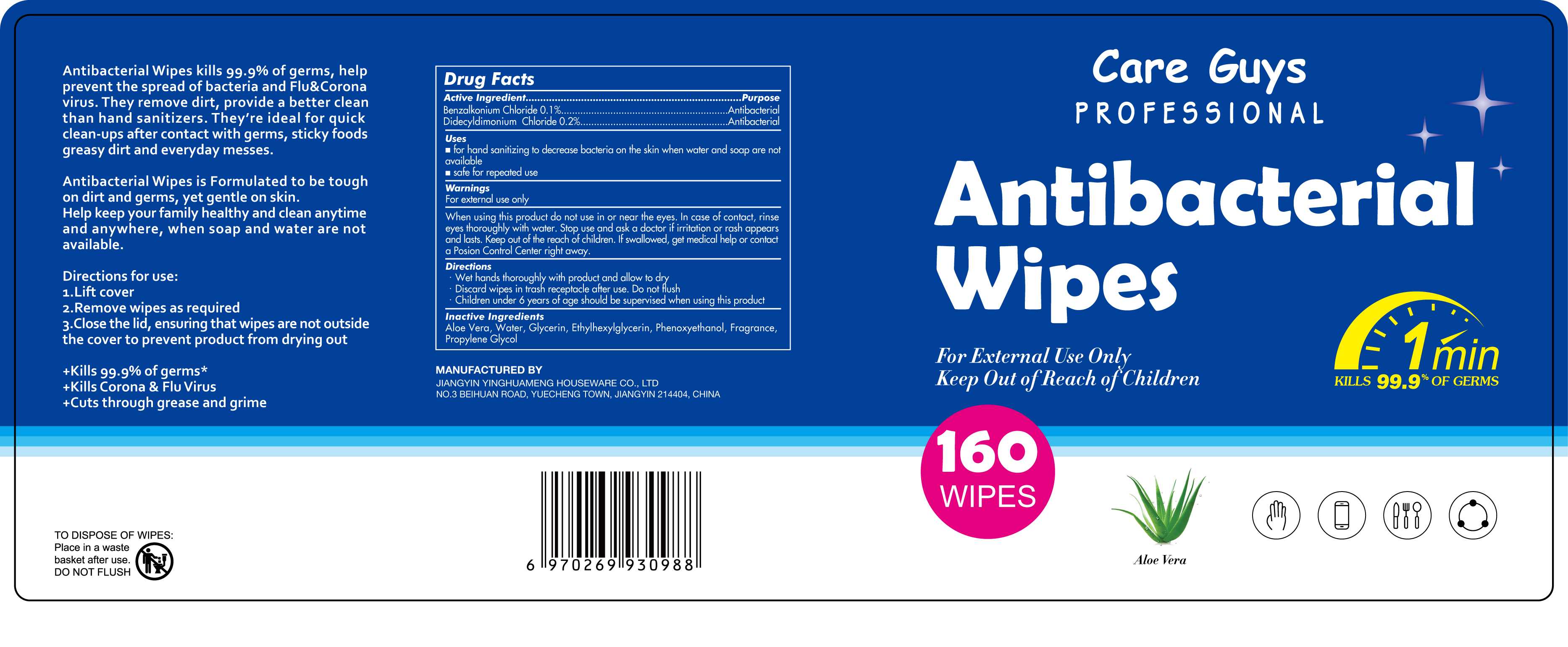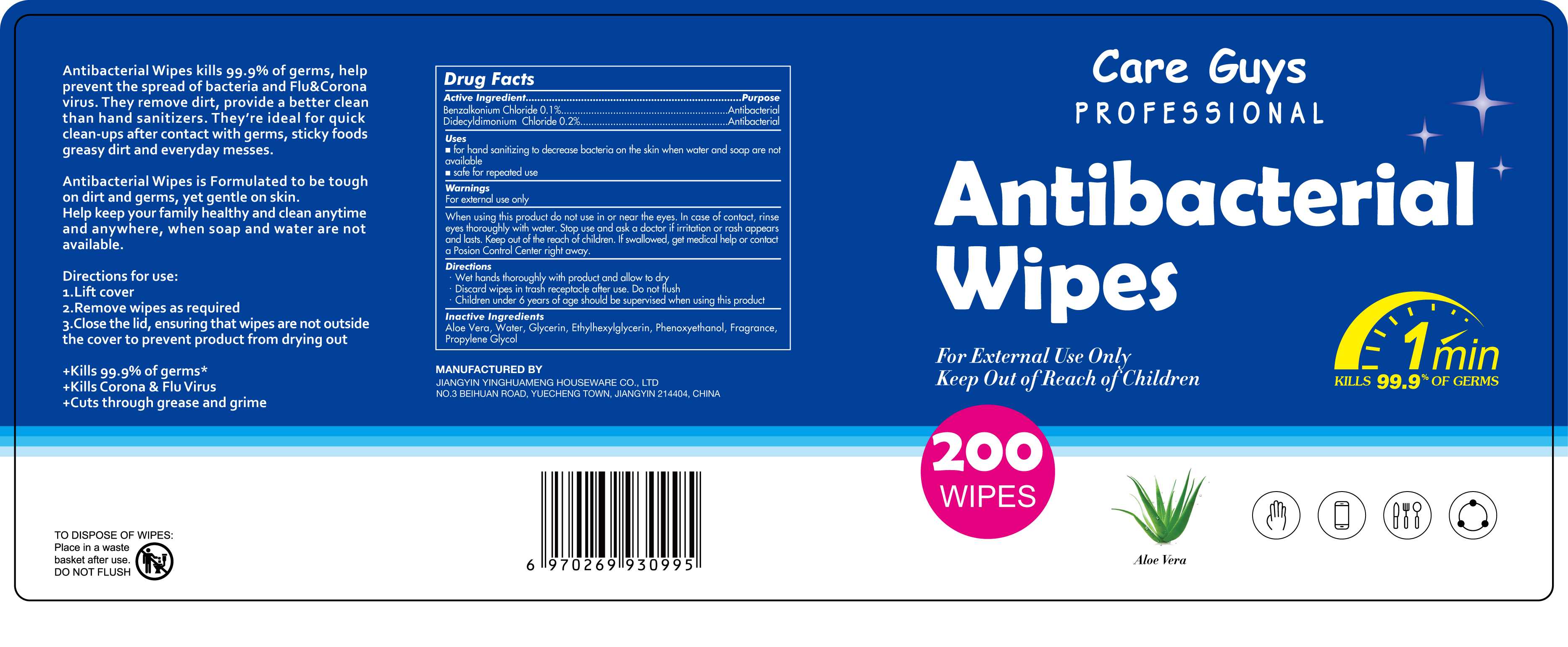 DRUG LABEL: Antibacterial Wipes
NDC: 75126-018 | Form: CLOTH
Manufacturer: Jiangyin Yinghuameng Houseware Co., Ltd.
Category: otc | Type: HUMAN OTC DRUG LABEL
Date: 20200903

ACTIVE INGREDIENTS: BENZALKONIUM CHLORIDE 0.1 g/100 1; DIDECYLDIMONIUM CHLORIDE 0.2 g/100 1
INACTIVE INGREDIENTS: GLYCERIN; WATER; PROPYLENE GLYCOL; ETHYLHEXYLGLYCERIN; PHENOXYETHANOL; FRAGRANCE LEMON ORC2001060; ALOE VERA LEAF

75126-018
Antibacterial Wipes

Active Ingredient(s)

Benzalkonium Chloride 0.1%
Didecyldimonium Chloride 0.2%

Purpose

Antibacterial

Use

for hand sanitizing to decrease bacteria on the skin when water and soap are not available
safe for repeated use

Warnings

For external use only

When using this product
do not use in or near the eyes. In case of contact, rinse eyes thoroughly with water.

Stop use and ask a doctor if irritation or rash appears and lasts.

Keep out of the reach of children. If swallowed, get medical help or contact a Posion Control Center right away.

do not use in or near the eyes. In case of contact, rinse eyes thoroughly with water.

When using this product
do not use in or near the eyes. In case of contact, rinse eyes thoroughly with water.

Stop use and ask a doctor if irritation or rash appears and lasts.

Keep out of the reach of children. If swallowed, get medical help or contact a Posion Control Center right away.

Stop use and ask a doctor if irritation or rash appears and lasts.

Directions

Wet hands thoroughly with product and allow to d r y · Discard wipes in trash receptacle after use. Do not Hush
Children under 6 years of age should be supervised when using this product

Other information

/

Inactive ingredients

Water, Glycerin, Propylene Glycol,
Aloe Vera, Ethylhexylglycerin, Phenoxyethanol,
Fragrance